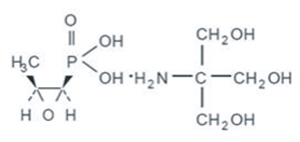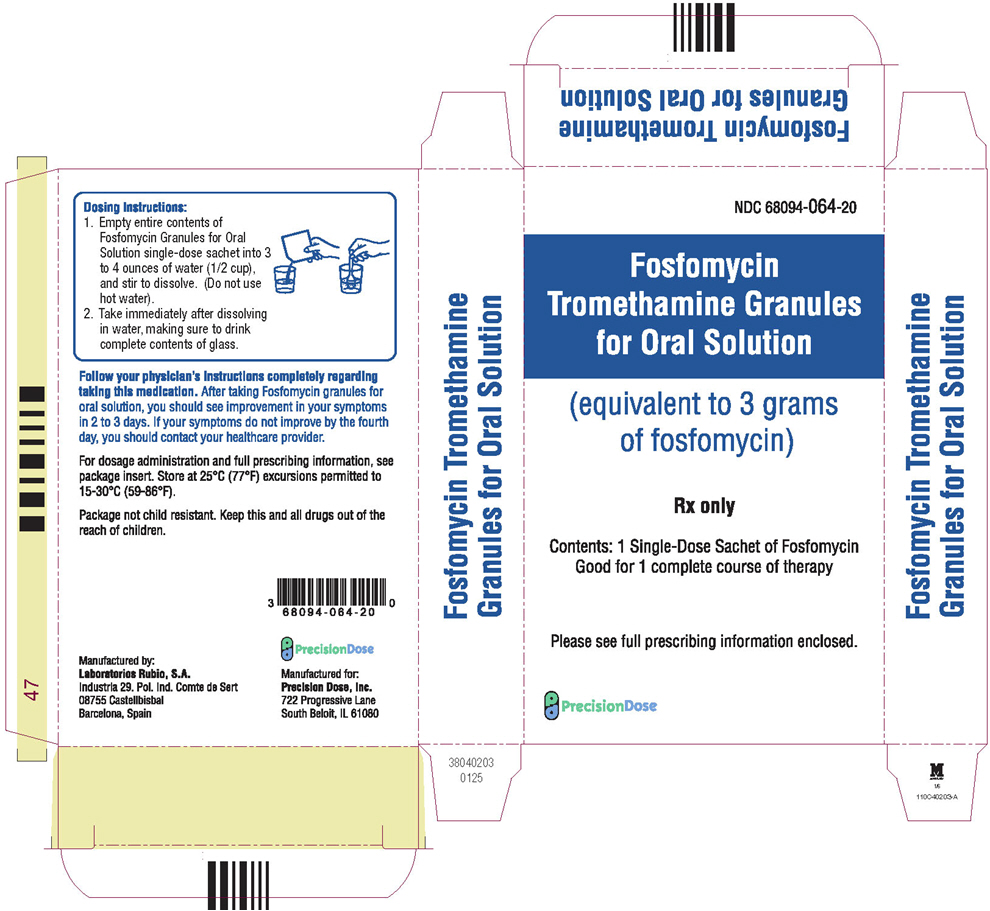 DRUG LABEL: Fosfomycin Tromethamine
NDC: 68094-064 | Form: GRANULE
Manufacturer: Precision Dose, Inc.
Category: prescription | Type: HUMAN PRESCRIPTION DRUG LABEL
Date: 20251223

ACTIVE INGREDIENTS: Fosfomycin Tromethamine 3 g/1 1
INACTIVE INGREDIENTS: Sucrose; Orange; Saccharin

Fosfomycin Tromethamine Granules for Oral Solution

Rx only

DESCRIPTION

Fosfomycin Tromethamine Granules for Oral Solution contains Fosfomycin Tromethamine, a synthetic, broad spectrum, bactericidal antibiotic for oral administration. It is available as a single dose sachet which contains white granules consisting of 5.631 grams of Fosfomycin Tromethamine (equivalent to 3 grams of fosfomycin), and the following inactive ingredients: orange ﬂavor, saccharin, and sucrose. The contents of the sachet must be dissolved in water. Fosfomycin Tromethamine, a phosphonic acid derivative, is available as (1R,2S)-(1,2-epoxypropyl)phosphonic acid, compound with 2-amino-2-(hydroxy-methyl)-1,3-propanediol (1:1). It is a white granular compound with a molecular weight of 259.2. Its empirical formula is C3H7O4P∙C4H11NO3, and its chemical structure is as follows:

CLINICAL PHARMACOLOGY

Absorption

Fosfomycin Tromethamine is rapidly absorbed following oral administration and converted to the free acid, fosfomycin. Absolute oral bioavailability under fasting conditions is 37%. After a single 3-gram dose of Fosfomycin Tromethamine Granules for Oral Solution, the mean (± 1 SD) maximum serum concentration (Cmax) achieved was 26.1 (± 9.1) mcg/mL within 2 hours. The oral bioavailability of fosfomycin is reduced to 30% under fed conditions. Following a single 3-gram oral dose of fosfomycin Tromethamine Granules for Oral Solution with a high-fat meal, the mean Cmax achieved was 17.6 (± 4.4) mcg/mL within 4 hours. Cimetidine does not affect the pharmacokinetics of Fosfomycin when co-administered with Fosfomycin Tromethamine Granules for Oral Solution. Metoclopramide lowers the serum concentrations and urinary excretion of fosfomycin when coadministered with Fosfomycin Tromethamine Granules for Oral Solution. (See PRECAUTIONS, Drug Interactions.)

Distribution

The mean apparent steady-state volume of distribution (Vss) is 136.1 (±44.1) L following oral administration of Fosfomycin Tromethamine Granules for Oral Solution. Fosfomycin is not bound to plasma proteins.

Fosfomycin is distributed to the kidneys, bladder wall, prostate, and seminal vesicles. Following a 50 mg/kg dose of fosfomycin to patients undergoing urological surgery for bladder carcinoma, the mean concentration of fosfomycin in the bladder, taken at a distance from the neoplastic site, was 18.0 mcg per gram of tissue at 3 hours after dosing. Fosfomycin has been shown to cross the placental barrier in animals and man.

Excretion

Fosfomycin is excreted unchanged in both urine and feces. Following oral administration of Fosfomycin Tromethamine Granules for Oral Solution, the mean total body clearance (CLTB) and mean renal clearance (CLR) of fosfomycin were 16.9 (± 3.5) L/hr and 6.3 (± 1.7) L/hr, respectively. Approximately 38% of a 3-gram dose of Fosfomycin Tromethamine Granules for Oral Solution is recovered from urine, and 18% is recovered from feces. Following intravenous administration, the mean CLTB and mean CLR of fosfomycin were 6.1 (±1.0) L/hr and 5.5 (± 1.2) L/hr, respectively.

A mean urine fosfomycin concentration of 706 (± 466) mcg/mL was attained within 2-4 hours after a single oral 3-gm dose of Fosfomycin Tromethamine Granules for Oral Solution under fasting conditions. The mean urinary concentration of fosfomycin was 10 mcg/mL in samples collected 72-84 hours following a single oral dose of Fosfomycin Tromethamine.

Following a 3-gram dose of Fosfomycin Tromethamine Granules for Oral Solution administered with a high fat meal, a mean urine fosfomycin concentration of 537 (± 252) mcg/mL was attained within 6-8 hours. Although the rate of urinary excretion of fosfomycin was reduced under fed conditions, the cumulative amount of fosfomycin excreted in the urine was the same, 1118 (± 201) mg (fed) vs. 1140 mg (± 238) (fasting). Further, urinary concentrations equal to or greater than 100 mcg/mL were maintained for the same duration, 26 hours, indicating that Fosfomycin Tromethamine Granules for Oral Solution can be taken without regard to food. Following oral administration of Fosfomycin Tromethamine Granules for Oral Solution the mean half-life for elimination (t1/2) is 5.7 (± 2.8) hours.

Special Populations

Geriatric

Based on limited data regarding 24-hour urinary drug concentrations, no differences in urinary excretion of fosfomycin have been observed in elderly subjects. No dosage adjustment is necessary in the elderly.

Gender

There are no gender differences in the pharmacokinetics of fosfomycin.

Renal Insufﬁciency

In 5 anuric patients undergoing hemodialysis, the t1/2 of fosfomycin during hemodialysis was 40 hours. In patients with varying degrees of renal impairment (creatinine clearances varying from 54 mL/min to 7 mL/min), the t1/2 of fosfomycin increased from 11 hours to 50 hours. The percent of fosfomycin recovered in urine decreased from 32% to 11% indicating that renal impairment signiﬁcantly decreases the excretion of fosfomycin.

Microbiology

Fosfomycin (the active component of Fosfomycin Tromethamine) has in vitro activity against a broad range of gram-positive and gram-negative aerobic microorganisms which are associated with uncomplicated urinary tract infections. Fosfomycin is bactericidal in urine at therapeutic doses. The bactericidal action of fosfomycin is due to its inactivation of the enzyme enolpyruvyl transferase, thereby irreversibly blocking the condensation of uridine diphosphate-N-acetylglucosamine with penolpyruvate, one of the ﬁrst steps in bacterial cell wall synthesis. It also reduces adherence of bacteria to uroepithelial cells.

There is generally no cross-resistance between fosfomycin and other classes of antibacterial agents such as beta-lactams and aminoglycosides. Fosfomycin has been shown to be active against most strains of the following microorganisms, both in vitro and in clinical infections as described in the INDICATIONS AND USAGE section:

Aerobic gram-positive microorganisms

Enterococcus faecalis

Aerobic gram-negative microorganisms

Escherichia coli

The following in vitro data are available, but their clinical signiﬁcance is unknown.

Fosfomycin exhibits in vitro minimum inhibitory concentrations (MIC's) of 64 mcg/mL or less against most (≥ 90%) strains of the following microorganisms; however, the safety and effectiveness of fosfomycin in treating clinical infections due to these microorganisms has not been established in adequate and well-controlled clinical trials:

Aerobic gram-positive microorganisms

Enterococcus faecium

Aerobic gram-negative microorganisms

Citrobacter diversus
Citrobacter freundii
Enterobacter aerogenes
Klebsiella oxytoca
Klebsiella pneuomoniae
Proteus mirabilis
Proteus vulgaris
Serratia marcescens

Susceptibility Testing

For speciﬁc information regarding susceptibility test interpretive criteria and associated test methods and quality control standards recognized by FDA for this drug, please see: https://www.fda.gov/STIC.

INDICATIONS AND USAGE

Fosfomycin Tromethamine is indicated only for the treatment of uncomplicated urinary tract infections (acute cystitis) in women due to susceptible strains of Escherichia coli and Enterococcus faecalis. Fosfomycin Tromethamine Granules for Oral Solution is not indicated for the treatment of pyelonephritis or perinephric abscess.

If persistence or reappearance of bacteriuria occurs after treatment with Fosfomycin Tromethamine, other therapeutic agents should be selected. (See PRECAUTIONS and CLINICAL STUDIES sections.)

CONTRAINDICATIONS

Fosfomycin Tromethamine Granules for Oral Solution is contraindicated in patients with known hypersensitivity to the drug.

WARNINGS

Clostridium difﬁcile associated diarrhea (CDAD) has been reported with use of nearly all antibacterial agents, including Fosfomycin Tromethamine Granules for Oral Solution, and may range in severity from mild diarrhea to fatal colitis. Treatment with antibacterial agents alters the normal ﬂora of the colon leading to overgrowth of C. difﬁcile.

C. difﬁcile produces toxins A and B which contribute to the development of CDAD. Hypertoxin producing strains of C. difﬁcile cause increased morbidity and mortality, as these infections can be refractory to antimicrobial therapy and may require colectomy. CDAD must be considered in all patients who present with diarrhea following antibiotic use. Careful medical history is necessary since CDAD has been reported to occur over two months after the administration of antibacterial agents.

If CDAD is suspected or conﬁrmed, ongoing antibiotic use not directed against C. difﬁcile may need to be discontinued. Appropriate ﬂuid and electrolyte management, protein supplementation, antibiotic treatment of C. difﬁcile, and surgical evaluation should be instituted as clinically indicated.

PRECAUTIONS

General

Do not use more than one single dose of Fosfomycin Tromethamine Granules for Oral Solution to treat a single episode of acute cystitis. Repeated daily doses of Fosfomycin Tromethamine Granules for Oral Solution did not improve the clinical success or microbiological eradication rates compared to single dose therapy but did increase the incidence of adverse events. Urine specimens for culture and susceptibility testing should be obtained before and after completion of therapy.

Information for Patients

Patients should be informed:

- That Fosfomycin Tromethamine Granules for Oral Solution can be taken with or without food.
- That their symptoms should improve in two to three days after taking Fosfomycin Tromethamine Granules for Oral Solution; if not improved, the patient should contact her health care provider.
- Diarrhea is a common problem caused by antibiotics which usually ends when the antibiotic is discontinued. Sometimes after starting treatment with antibiotics, patients can develop watery and bloody stools (with or without stomach cramps and fever) even as late as two or more months after having taken the last dose of the antibiotic. If this occurs, patients should contact their physician as soon as possible.

Drug Interactions

Metoclopramide

When coadministered with Fosfomycin Tromethamine Granules for Oral Solution, metoclopramide, a drug which increases gastrointestinal motility, lowers the serum concentration and urinary excretion of fosfomycin. Other drugs that increase gastrointestinal motility may produce similar effects.

Cimetidine

Cimetidine does not affect the pharmacokinetics of fosfomycin when coadministered with Fosfomycin Tromethamine Granules for Oral Solution.

Carcinogenesis, Mutagenesis, Impairment of Fertility

Long term carcinogenicity studies in rodents have not been conducted because Fosfomycin Tromethamine Granules for Oral Solution is intended for single dose treatment in humans. Fosfomycin Tromethamine Granules for Oral Solution was not mutagenic or genotoxic in the in vitro Ames' bacterial reversion test, in cultured human lymphocytes, in Chinese hamster V79 cells, and the in vivo mouse micronucleus assay. Fosfomycin Tromethamine Granules for Oral Solution did not affect fertility or reproductive performance in male and female rats.

Pregnancy

Teratogenic Effects

When administered intramuscularly as the sodium salt at a dose of 1 gram to pregnant women, fosfomycin crosses the placental barrier. Fosfomycin Tromethamine Granules for Oral Solution crosses the placental barrier of rats; it does not produce teratogenic effects in pregnant rats at dosages as high as 1000 mg/kg/day (approximately 9 and 1.4 times the human dose based on body weight and mg/m^2, respectively). When administered to pregnant female rabbits at dosages as high as 1000 mg/kg/day (approximately 9 and 2.7 times the human dose based on body weight and mg/m^2, respectively), fetotoxicities were observed. However, these toxicities were seen at maternally toxic doses and were considered to be due to the sensitivity of the rabbit to changes in the intestinal microﬂora resulting from the antibiotic administration. There are, however, no adequate and well-controlled studies in pregnant women. Because animal reproduction studies are not always predictive of human response, this drug should be used during pregnancy only if clearly needed.

Nursing Mothers

It is not known whether fosfomycin Tromethamine is excreted in human milk. Because many drugs are excreted in human milk and because of the potential for serious adverse reactions in nursing infants from Fosfomycin Tromethamine Granules for Oral Solution, a decision should be made whether to discontinue nursing or to not administer the drug, taking into account the importance of the drug to the mother.

Pediatric Use

Safety and effectiveness in children age 12 years and under have not been established in adequate and well-controlled studies.

Geriatric Use

Clinical studies of Fosfomycin Tromethamine Granules for Oral Solution did not include sufﬁcient numbers of subjects aged 65 and over to determine whether they respond differently from younger subjects. Other reported clinical experience has not identiﬁed differences in responses between the elderly and younger patients. In general, dose selection for an elderly patient should be cautious, usually starting at the low end of the dosing range, reﬂecting the greater frequency of decreased hepatic, renal, or cardiac function, and of concomitant disease or other drug therapy.

ADVERSE REACTIONS

Clinical Trials

In clinical studies, drug related adverse events which were reported in greater than 1% of the fosfomycin-treated study population are listed below:

Drug-Related Adverse Events (%) in Fosfomycin and Comparator Populations
Adverse Events | Fosfomycin N = 1233 | Nitrofurantoin N = 374 | Trimethoprim/Sulfamethoxazole N = 428 | Ciprofloxacin N = 455
Diarrhea | 9.0 | 6.4 | 2.3 | 3.1
Vaginitis | 5.5 | 5.3 | 4.7 | 6.3
Nausea | 4.1 | 7.2 | 8.6 | 3.4
Headache | 3.9 | 5.9 | 5.4 | 3.4
Dizziness | 1.3 | 1.9 | 2.3 | 2.2
Asthenia | 1.1 | 0.3 | 0.5 | 0.0
Dyspepsia | 1.1 | 2.1 | 0.7 | 1.1

In clinical trials, the most frequently reported adverse events occurring in > 1% of the study population regardless of drug relationship were: diarrhea 10.4%, headache 10.3%, vaginitis 7.6%, nausea 5.2%, rhinitis 4.5%, back pain 3.0%, dysmenorrheal 2.6%, pharyngitis 2.5%, dizziness 2.3%, abdominal pain 2.2%, pain 2.2%, dyspepsia 1.8%, asthenia 1.7%, and rash 1.4%.

The following adverse events occurred in clinical trials at a rate of less than 1%, regardless of drug relationship: abnormal stools, anorexia, constipation, dry mouth, dysuria, ear disorder, fever, ﬂatulence, ﬂu syndrome, hematuria, infection, insomnia, lymphadenopathy, menstrual disorder, migraine, myalgia, nervousness, paresthesia, pruritus, SGPT increased, skin disorder, somnolence, and vomiting.

One patient developed unilateral optic neuritis, an event considered possibly related to Fosfomycin Tromethamine Granules for Oral Solution therapy.

Post-marketing Experience

Serious adverse events from the marketing experience with Fosfomycin Tromethamine Granules for Oral Solution outside of the United States have been rarely reported and include angioedema, aplastic anemia, asthma (exacerbation), cholestatic jaundice, hepatic necrosis, and toxic megacolon. Although causality has not been established, during post-marketing surveillance, the following events have occurred in patients prescribed Fosfomycin Tromethamine: anaphylaxis and hearing loss.

Laboratory Changes

Signiﬁcant laboratory changes reported in U.S. clinical trials of Fosfomycin Tromethamine Granules for Oral Solution without regard to drug relationship include: increased eosinophil count, increased or decreased WBC count, increased bilirubin, increased SGPT, increased SGOT, increased alkaline phosphatase, decreased hematocrit, decreased hemoglobin, increased and decreased platelet count. The changes were generally transient and were not clinically signiﬁcant.

To report SUSPECTED ADVERSE REACTIONS, contact Precision Dose, Inc. at 1-800-397-9228 or FDA at 1-800-FDA-1088 or www.fda.gov/medwatch.

OVERDOSAGE

In acute toxicology studies, oral administration of high doses of Fosfomycin Tromethamine Granules for Oral Solution up to 5 g/kg were well tolerated in mice and rats, produced transient and minor incidences of watery stools in rabbits, and produced diarrhea with anorexia in dogs occurring 2-3 days after single dose administration. These doses represent 50-125 times the human therapeutic dose.

The following events have been observed in patients who have taken Fosfomycin Tromethamine Granules for Oral Solution in overdose: vestibular loss, impaired hearing, metallic taste, and general decline in taste perception. In the event of overdosage, treatment should be symptomatic and supportive.

DOSAGE AND ADMINISTRATION

The recommended dosage for women 18 years of age and older for uncomplicated urinary tract infection (acute cystitis) is one sachet of Fosfomycin Tromethamine Granules for Oral Solution. Fosfomycin Tromethamine Granules for Oral Solution may be taken with or without food. Fosfomycin Tromethamine Granules for Oral Solution should not be taken in its dry form. Always mix Fosfomycin Tromethamine Granules for Oral Solution with water before ingesting. (See PREPARATION section.)

PREPARATION

Fosfomycin Tromethamine Granules for Oral Solution should be taken orally. Pour the entire contents of a single-dose sachet of Fosfomycin Tromethamine Granules for Oral Solution into 3 to 4 ounces of water (1/2 cup) and stir to dissolve. Do not use hot water. Fosfomycin Tromethamine Granules for Oral Solution should be taken immediately after dissolving in water.

HOW SUPPLIED

Fosfomycin Tromethamine Granules for Oral Solution is available as a single-dose sachet containing the equivalent of 3 grams of Fosfomycin.

 | NDC
Single-dose sachet | 68094-064-01
One unit carton | 68094-064-20

STORAGE AND HANDLING

Store at 25°C (77°F); excursions permitted to 15-30°C (59-86°F). Keep this and all drugs out of the reach of children.

CLINICAL STUDIES

In controlled, double-blind studies of acute cystitis performed in the United States, a single dose of Fosfomycin Tromethamine Granules for Oral Solution was compared to three other oral antibiotics (See table below). The study population consisted of patients with symptoms and signs of acute cystitis of less than 4 days duration, no manifestations of upper tract infection (e.g., ﬂank pain, chills, fever), no history of recurrent urinary tract infections (20% of patients in the clinical studies had a prior episode of acute cystitis within the preceding year), no known structural abnormalities, no clinical or laboratory evidence of hepatic dysfunction, and no known or suspected CNS disorders, such as epilepsy, or other factors which would predispose to seizures. In these studies, the following clinical success (resolution of symptoms) and microbiologic eradication rates were obtained.

Treatment Arm | Treatment Duration | Microbiologic Eradication Rate |  | Clinical Success Rate | Outcome (based on difference in microbiologic eradication rates 5-11 days posttherapy
Treatment Arm | (Days) | 5-11 days post therapy | Study day 12-21 | Clinical Success Rate | Outcome (based on difference in microbiologic eradication rates 5-11 days posttherapy
Fosfomycin | 1 | 630/771 (82%) | 591/771 (70%) | 542/771 (70%)
Ciprofloxacin | 7 | 219/222 (98%) | 219/222 (98%) | 213/222 (96%) | Fosfomycin inferior to Ciprofloxacin
Trimethoprim/ Sulfamethoxazole | 10 | 194/197 (98%) | 194/197 (98%) | 186/197 (94%) | Fosfomycin inferior to trimethoprim/Sulfamethoxazole
Nitrofurantoin | 7 | 180/238 (76%) | 180/238 (76%) | 183/238 (77%) | Fosfomycin equivalent to nitrofurantion

Pathogen | Fosfomycin 3 gram single dose | Ciprofloxacin 250 mg Bid × 7 days | Trimethoprim/Sulfamethoxazole 160 mg/800 mg bid × 10 days | Nitrofurantoin 100 mg Bid × 7 days
E. coli | 509/644 (79%) | 184/187 (98%) | 171/174 (98%) | 146/187 (78%)
E. Faecalis | 10/10 (100%) | 0/0 | 4/4 (100%) | 1/2 (50%)

REFERENCES

1. National Committee for Clinical Laboratory Standards, Methods for Dilution.
  Antimicrobial Susceptibility Tests for Bacteria that Grow Aerobically – Third Edition; Approved Standard NCCLS Document M7-A3, Vol. 13, No. 25 NCCLS, Villanova, PA, December, 1993.
2. National Committee for Clinical Laboratory Standards, Performance Standard for Antimicrobial Disk Susceptibility Tests – Fifth Edition; Approved Standard
  NCCLS Document M2-A5, Vol. 13, No. 24 NCCLS, Villanova, PA, December 1993.

Manufactured by:
Laboratorios Rubio, S.A.
Industria 29. Pol. Ind. Comte de Sert
08755 Castellbisbal Barcelona, Spain

Distributed by:
Precision Dose, Inc.
722 Progressive Lane,
South Beloit, IL 61080

Rev. June 2025

36142101 0125

PRINCIPAL DISPLAY PANEL - 3 gram Sachet Carton

NDC 68094-064-20

Fosfomycin
Tromethamine Granules
for Oral Solution

(equivalent to 3 grams
of fosfomycin)

Rx only

Contents: 1 Single-Dose Sachet of Fosfomycin
Good for 1 complete course of therapy

Please see full prescribing information enclosed.

Precision Dose